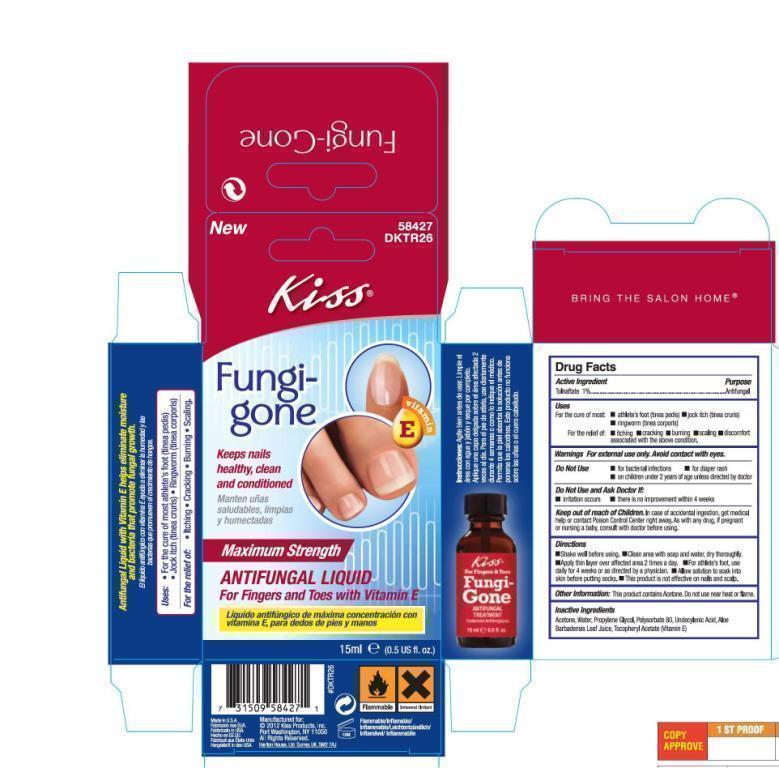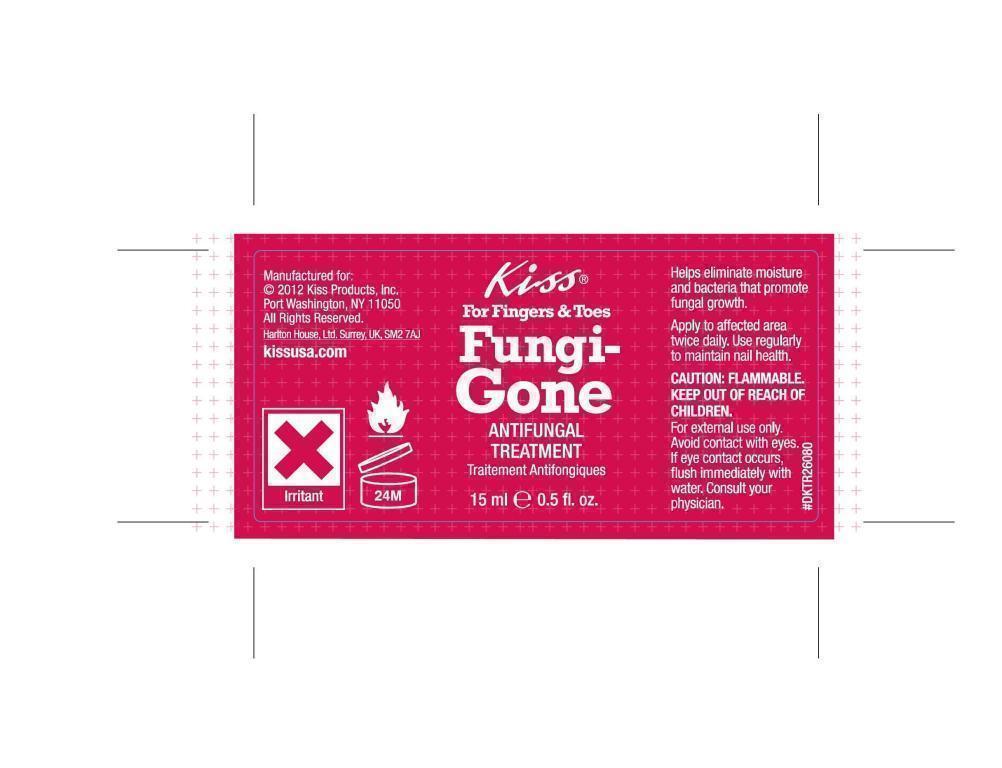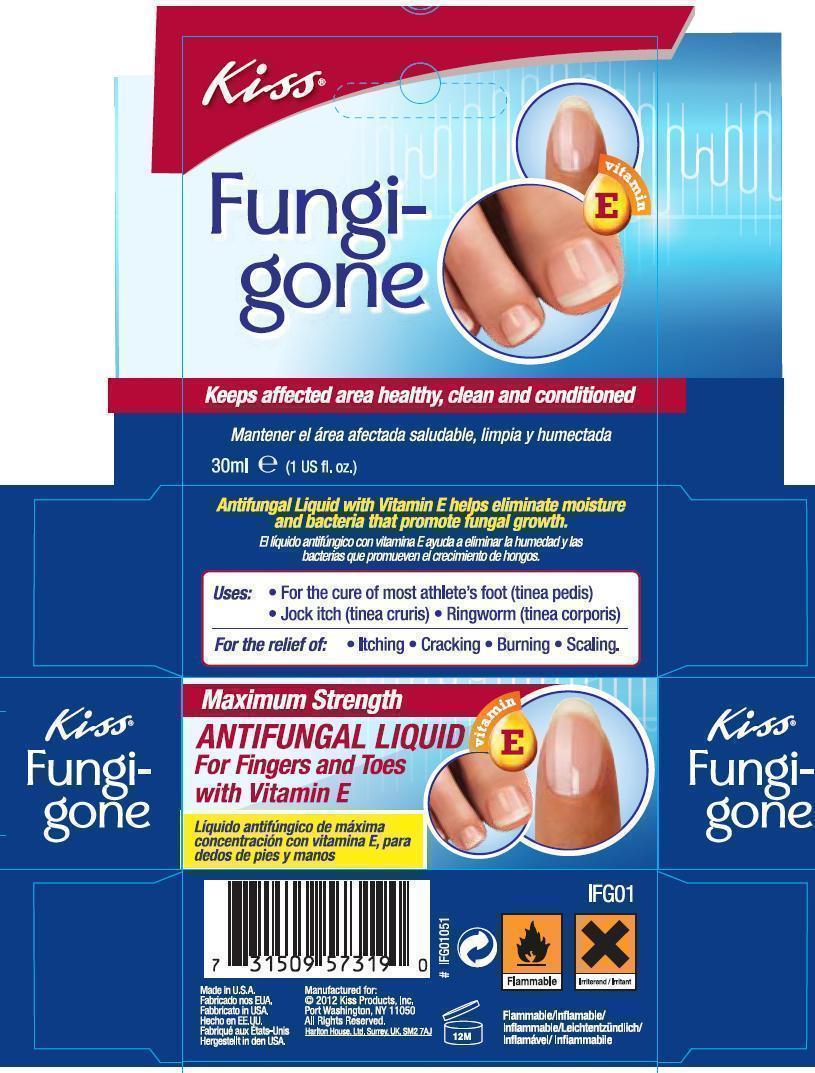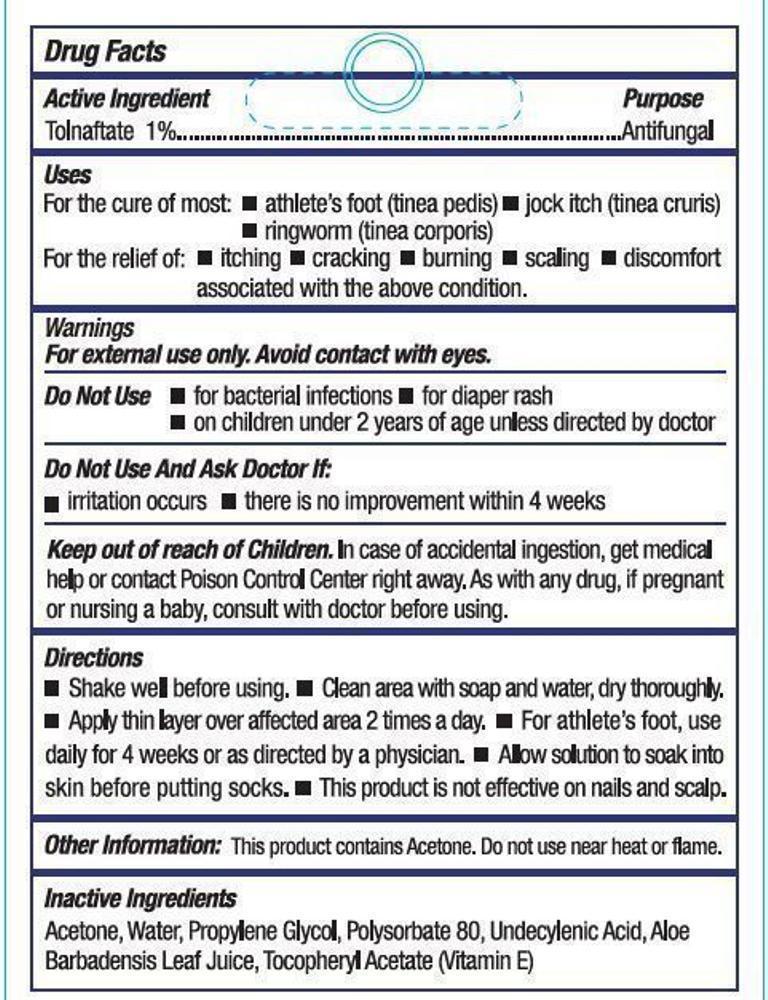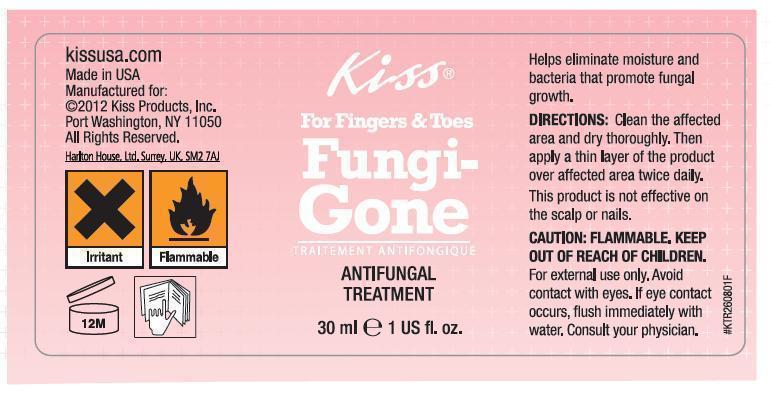 DRUG LABEL: Kiss Fungi-Gone
NDC: 42432-101 | Form: LIQUID
Manufacturer: Kiss Products, Inc.
Category: otc | Type: HUMAN OTC DRUG LABEL
Date: 20150225

ACTIVE INGREDIENTS: TOLNAFTATE 10 mg/1 mL
INACTIVE INGREDIENTS: ACETONE; PROPYLENE GLYCOL; WATER; POLYSORBATE 80; UNDECYLENIC ACID; ALOE VERA LEAF; ALPHA-TOCOPHEROL ACETATE

Kiss Fungi-Gone Antifungal Treatment - Drug Facts

Active Ingredient

Tolnaftate 1%

Purpose

Anti-fungal

Uses

For the cure of:

- athlete's foot (tinea pedis)
- jock itch (tinea cruris)
- ringworm (tinea corporis)

For the relief of:

- itching
- cracking
- burning
- scaling
- discomfort associated with the above condition

Warnings

For external use only. Avoid contact with eyes.

Do not use

- for bacterial infections
- for diaper rash
- on children under 2 years of age unless directed by a doctor

Do not use and ask doctor if:

- irritation occurs
- there is no improvement within 4 weeks

KEEP OUT OF REACH OF CHILDREN.

In case of accidental ingestion, get medical help or contact Poison
Control Center right away. As with any drug, if pregnant or nursing a baby, consult with a doctor before using.

Directions

- Shake well before using
- Clean area with soap and water, dry thoroughly
- Apply thin layer over affected area 2 times a day
- For athlete's foot, use daily for 4 weeks or as directed by a physician
- Allow solution to soak into the skin before putting socks on
- This product is not effective on nails and scalp

Other Information

This product contains Acetone. Do not use near heat or flame.

Inactive Ingredients

Acetone, Water, Propylene Glycol, Polysorbate 80, Undecylenic Acid, Aloe Barbadensis Leaf Juice, Tocopheryl Acetate (Vitamin E)

Image of Labels and Cartons

FungiGoneHalfOunceLabel.jpg FungiGoneHalfOunceCarton.jpg FungiGoneOneOunceLabel.jpg FungiGoneOneOunceCarton1.jpg FungiGoneOneOunceCarton2.jpg